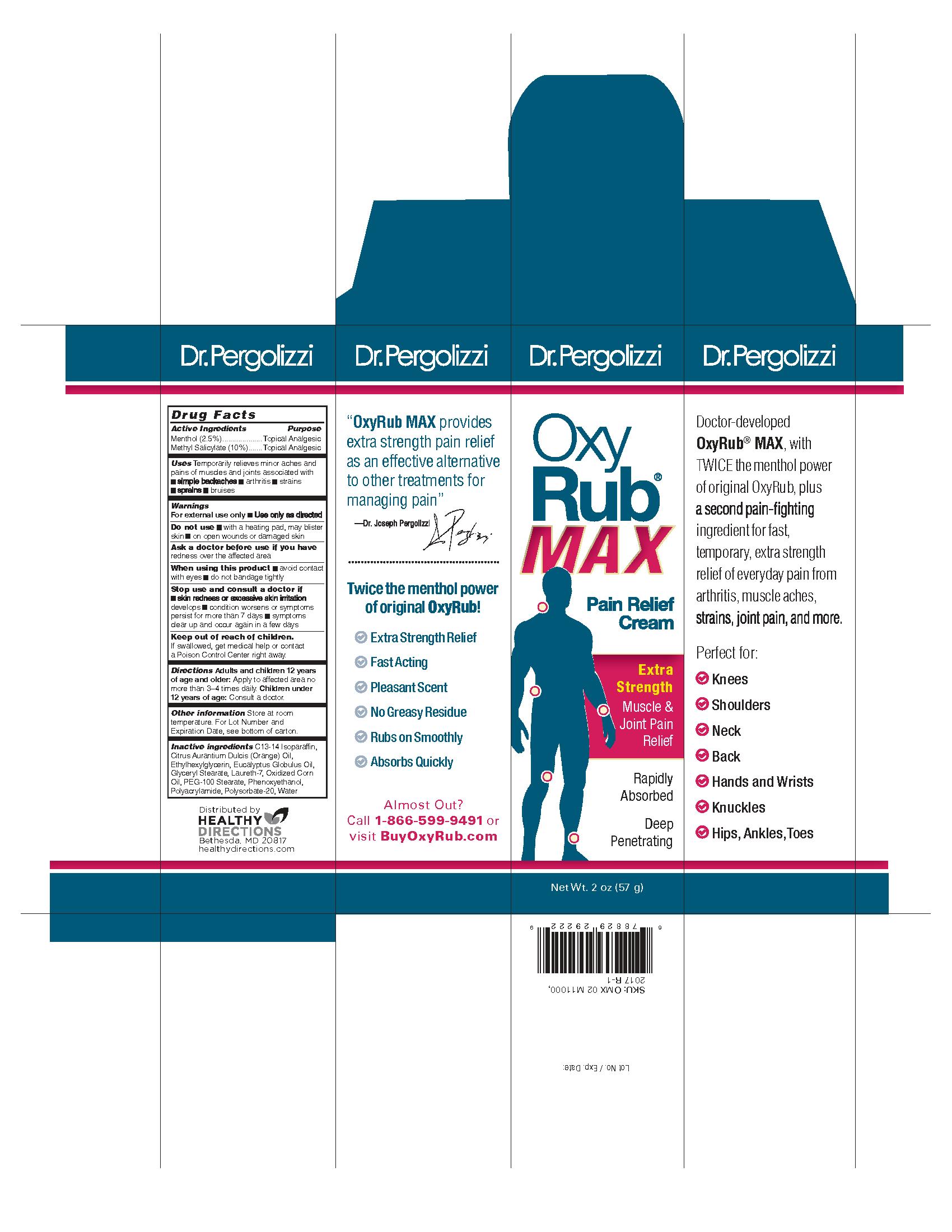 DRUG LABEL: OxyRub Max Pain Relief
NDC: 70015-650 | Form: CREAM
Manufacturer: Healthy Directions, LLC
Category: otc | Type: HUMAN OTC DRUG LABEL
Date: 20170502

ACTIVE INGREDIENTS: MENTHOL 25.0 mg/1 g; METHYL SALICYLATE 100.0 mg/1 g
INACTIVE INGREDIENTS: C13-16 ISOPARAFFIN; ORANGE OIL; ETHYLHEXYLGLYCERIN; EUCALYPTUS OIL; GLYCERYL MONOSTEARATE; LAURETH-7; CORN OIL; PEG-100 STEARATE; PHENOXYETHANOL; POLYACRYLAMIDE (CROSSLINKED; 0.01-0.2 MOLE PERCENT BISACRYLAMIDE); POLYSORBATE 20; WATER

OxyRub MAX Pain Relief Cream, 2oz

Drug Facts

Active Ingredients

Methol (2.5%)

Methyl Salicylate (10%)

Purpose

Topical Analgesic

Uses

Temporarily relieves minor aches and pains of muscles and joints associated with:

- simple backaches
- arthritis
- strains
- sprains
- bruises

Warnings

For external use only:Use only as directed

Do not use

- with a heating pad, may blister skin
- on open wounds or damaged skin

Ask a doctor before use if you have redness over the affected area

When using this product

- avoid contact with eyes
- do not bandage tightly

Stop use and consult a doctor if

- skin redness or excessive skin irritation developments
- condition worsens or symptoms persist for more than 7 days
- symptoms clear up and occur again in a few days

Keep out of reach of children.

If swallowed, get medical help or contact a Poison Control Center right away.

Directions

Adults and children 12 years of age and older: Apply to affected area no

more than 3-4 times daily. Children under 12 years of age: Consult a doctor.

Other information

Store at room termperature. For Lot Number and Expiration Date, see bottom of the carton.

Inactive ingredients C13-14, Insoaraffin,

Citrus Aurantium Dulcis (Organe) Oil,

Ehtylhexlglycerin, Eucalyptus Globulus Oil,

Glyceryl Stearate, Laureth-7, Oxidized Corn

Oil, PEG-100 Stearate, Phenoxyethanol,

Polyacrylamide, Polysorbate-20, Water

PACKAGE LABEL

Dr. Perigolizzi

OxyRub

MAX

Pain Relief Cream

Extra Strength

Muscle & Joint Pain Relief

Rapidly Absorbed

Deep Penetrating

Distributed by

HEALTHY DIRECTIONS

Bethesda, MD 20817

healthydirections.com